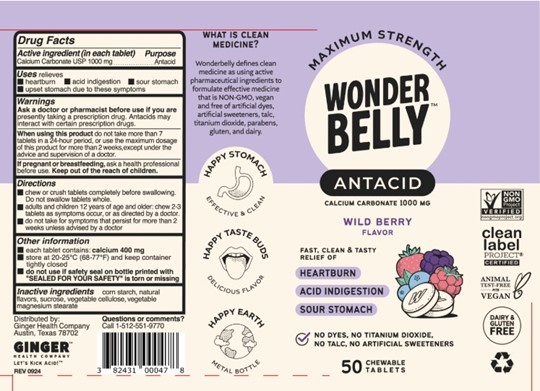 DRUG LABEL: WONDERBELLY MAXIMUM STRENGTH ANTACID
NDC: 82431-108 | Form: TABLET, CHEWABLE
Manufacturer: Ginger Health Company
Category: otc | Type: HUMAN OTC DRUG LABEL
Date: 20260401

ACTIVE INGREDIENTS: CALCIUM CARBONATE 1000 mg/1 1
INACTIVE INGREDIENTS: MAGNESIUM STEARATE; SUCROSE; STARCH, CORN; MICROCRYSTALLINE CELLULOSE

Wild Berry Antacid

Drug Facts

Active Ingredient (in each tablet)

Calcium Carbonate USP 1000 mg

Purpose

Antacid

Uses

relieves

- heartburn
- acid indigestion
- sour stomach
- upset stomach due to these symptoms

Warnings

Ask a doctor or pharmacist before use if you are

presently taking a prescription drug. Antacids may interact with certain prescription drugs.

When using this product

do not take more than 7 tablets in a 24-hour period, or use the maximum dosage of this product for more than 2 weeks, except under the advice and supervision of a doctor

If pregnant or breastfeeding,

ask a health professional before use.

Keep out of the reach of children.

Directions

- chew or crush tablets completely before swallowing. Do not swallow tablets whole.
- adults and children 12 years of age or older: chew 2-3 tablets as symptoms occur, or as directed by a doctor.
- do not take for symptoms that persist for more than 2 weeks unless advised by a doctor

Other information

- each tablet contains: calcium 400 mg
- store at 20-25°C (68-77°F) and keep container tightly closed
- do not use if safety seal on bottle printed with "SEALED FOR YOUR SAFETY" is torn or missing

Inactive ingredients

corn starch, natural flavors, sucrose, vegetable cellulose, vegetable magnesium stearate

Questions or comments?

Call 1-512-551-9770

Distributed by:

Ginger Health Company

Austin, Texas 78702

Principal Display Panel

Maximum Strength

WONDERBELLY

Antacid

Calcium Carbonate 1000 mg

WILD BERRY FLAVOR

Fast, Clean & Tasty Relief of

Heartburn

Acid Indigestion

Sour Stomach

No Dyes, No Titanium Dioxide, No Talc, No Artificial Sweeteners

50 Chewable Tablets